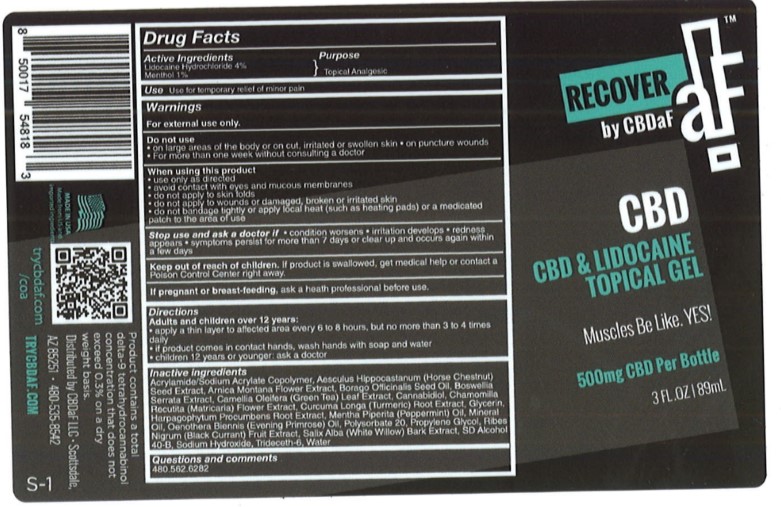 DRUG LABEL: CBDaF
NDC: 58443-0366 | Form: GEL
Manufacturer: Prime Enterprises
Category: otc | Type: HUMAN OTC DRUG LABEL
Date: 20201013

ACTIVE INGREDIENTS: MENTHOL 9.62 mg/1 mL; LIDOCAINE HYDROCHLORIDE 38.48 mg/1 mL
INACTIVE INGREDIENTS: ACRYLAMIDE; SODIUM ACRYLATE; CAMELLIA OLEIFERA LEAF; WATER; TRIDECETH-6; CHAMOMILE; MINERAL OIL; SODIUM HYDROXIDE; HORSE CHESTNUT; PEPPERMINT OIL; ARNICA MONTANA FLOWER; HARPAGOPHYTUM PROCUMBENS ROOT; SALIX ALBA BARK; BORAGE SEED OIL; TURMERIC; PROPYLENE GLYCOL; INDIAN FRANKINCENSE; BLACK CURRANT; ALCOHOL; EVENING PRIMROSE OIL; POLYSORBATE 20; CANNABIDIOL; GLYCERIN

CBDaF CBD & Lidocaine Topical Gel

Active Ingredients

Lidocaine Hydrochloride 4%, Menthol 1%

Purpose

Topical Analgesic

Uses

Use for temporary relief of minor pain

Warnings

For external use only.

Do not use

On large areas of the body or on cut, irritated or swollen skin

On puncture wounds

For more than one week without consulting a doctor

When using this product

Use only as directed

Avoid contact with eyes and mucous membranes

Do not apply to skin folds

Do not apply to wounds or damaged, broken or irritated skin

Do not bandage tightly or apply local heat (such as heating pads) or a medicated patch to the area of use

Stop use and ask doctor if

condition worses

irriation develops

redness appears

symptoms persist for more than 7 days or clear up and occurs again within a few days

Kepp out of reach of children

If product is swallowed, get medical help or contact a Poison Control Center right away.

If pregnant or breast-feeding

ask a health professional before use.

Directions

Adults and children over 12 years:

apply a thin layer to affected area every 6 to 8 hours, but no more than 3 to 4 times daily

if product comes in contact hands, wash hands with soap and water

children 12 years or younger: ask a doctor

Inactive ingredients

Acrylamide/Sodium Acrylate Copolymer, Aesculus Hippocastanum (Horse Chestnut) Seed Extract, Arnica Montana Flower Extract, Borago Officinalis Seed Oil, Boswellia Serrata Extract, Camellia Oleifera (Green Tea) Leaf Extract, Cannabidiol, Chamomilla Recutita (Matricaria) Flower Extract, Curcuma Longa (Turmeric) Root Extract, Glycerin, Harpagophytum Procumbens Root Extract, Mentha Piperita (Peppermint) Oil, Mineral Oil, Oenothera Biennis (Evening Primrose) Oil, Polysorbate 20, Propylene Glycol, Ribes Nigrum (Black Currant) Fruit Extract, Salix Alba (White Willow) Bark Extract, SD Alcohol 40-B, Sodium Hydroxide, Trideceth-6, Water

Questions and comments

480.562.6282